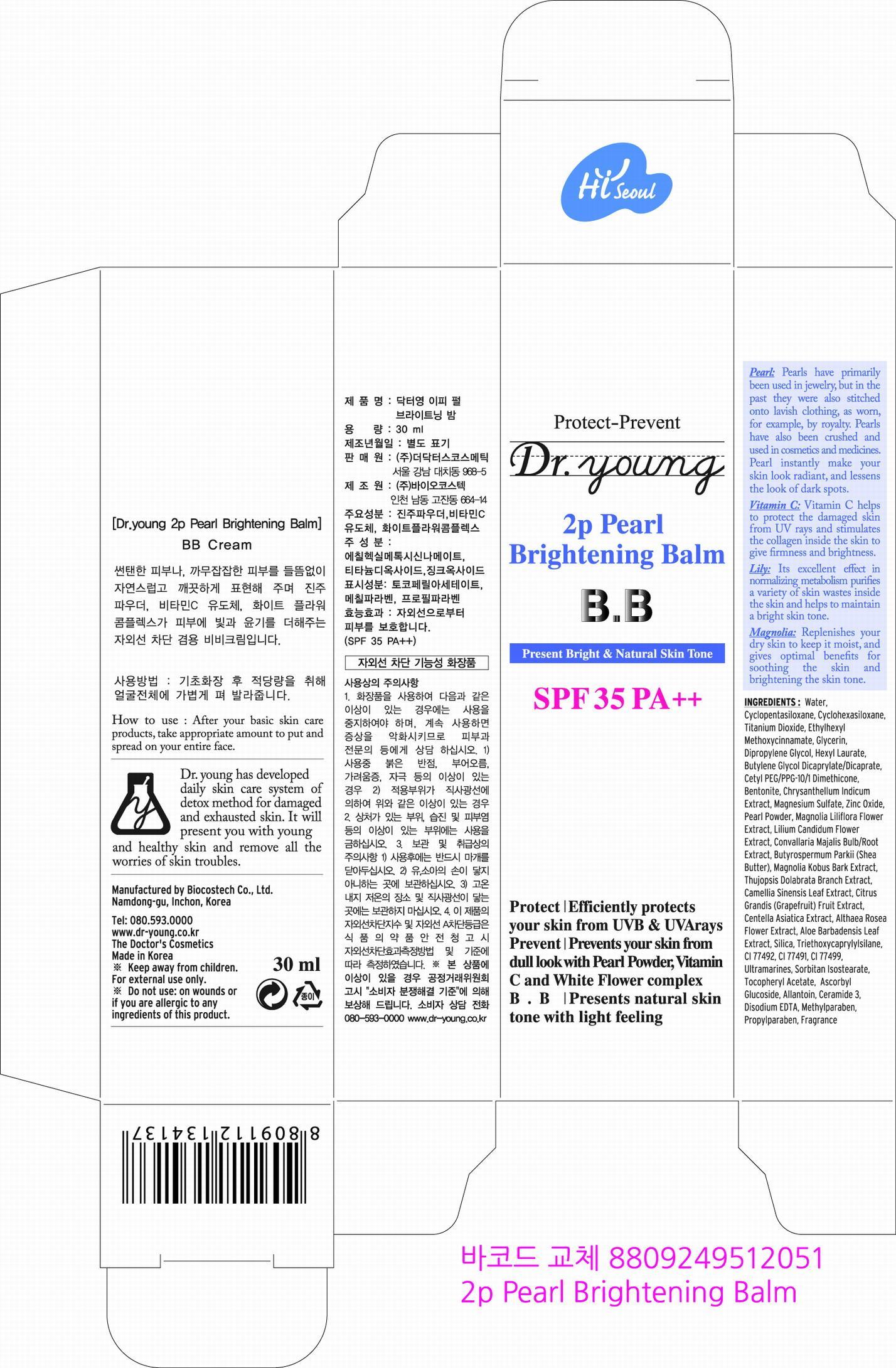 DRUG LABEL: Dr. Young 2P Pearl Brightening Balm SPF35 PA
NDC: 43948-1101 | Form: CREAM
Manufacturer: The Doctors Cosmetics Co., Ltd
Category: otc | Type: HUMAN OTC DRUG LABEL
Date: 20120925

ACTIVE INGREDIENTS: ALLANTOIN 0.5 mg/100 mL
INACTIVE INGREDIENTS: CYCLOMETHICONE 5; CYCLOMETHICONE 6; TITANIUM DIOXIDE; OCTINOXATE; GLYCERIN; DIPROPYLENE GLYCOL; HEXYL LAURATE; BUTYLENE GLYCOL DICAPRYLATE/DICAPRATE; CETYL PEG/PPG-10/1 DIMETHICONE (HLB 1.5); BENTONITE; CHRYSANTHELLUM INDICUM FLOWER OIL; MAGNESIUM SULFATE; ZINC OXIDE; MAGNOLIA LILIIFLORA FLOWER; CONVALLARIA MAJALIS BULB; SHEA BUTTER; MAGNOLIA KOBUS BARK; THUJOPSIS DOLABRATA WHOLE; BANCHA TEA LEAF/TWIG; PUMMELO; CENTELLA ASIATICA; ALCEA ROSEA FLOWER; ALOE VERA LEAF; TRIETHOXYCAPRYLYLSILANE; FERRIC OXIDE YELLOW; FERRIC OXIDE RED; FERROSOFERRIC OXIDE; SORBITAN ISOSTEARATE; .ALPHA.-TOCOPHEROL ACETATE; ASCORBYL GLUCOSIDE; LILIUM CANDIDUM FLOWER; CERAMIDE 3; METHYLPARABEN; PROPYLPARABEN

Drug Facts

ACTIVE INGREDIENT

allantoin

INACTIVE INGREDIENT

water, cyclopentasiloxane, cyclohexasiloxane, titanium dioxide, ethylhexyl methoxycinnamate, glycerin, dipropylene glycol, hexyl laurate, butylene glycol dicaprylate / dicaprate, cytyl peg/ppg-10/1 dimethicone, bentonite, chrysanthellum indicum extract, magnesium sulfate, zinc oxide, pearl powder, magnolia liliflora flower extract, lilium candidum flower extract, convallaria majalis bulb/root extract, shea butter, magnolia kobus bark extract, ghujopsis dolabrata branch extract, camellia sinensis leaf extract, grapefruit fruit extract, centella asiatica extract, althaea rosea flower extract, aloe barbadensis leaf extract, silica, triethoxycaprylsilane, ci 77492, ci 77491, ci 44299, ultramarines, sorbitan siostearate, tocopheryl acetate, ascorbyl glucoside, lilium candidum flower extract, ceramide 3, disodium edta, methylparaben, propylparaben, fragrance

PURPOSE

UVB, UVA protection

keep out of reach of the children

INDICATIONS AND USAGE

After basic skin care routine, apply evenly to your face

When using this product
- keep out of eyes, ears, and mouth. If contact occurs, rinse with plenty of cold water right away and contact a physician. If swallowing, drink plenty of water and contact a physician

DOSAGE AND ADMINISTRATION

for external use only